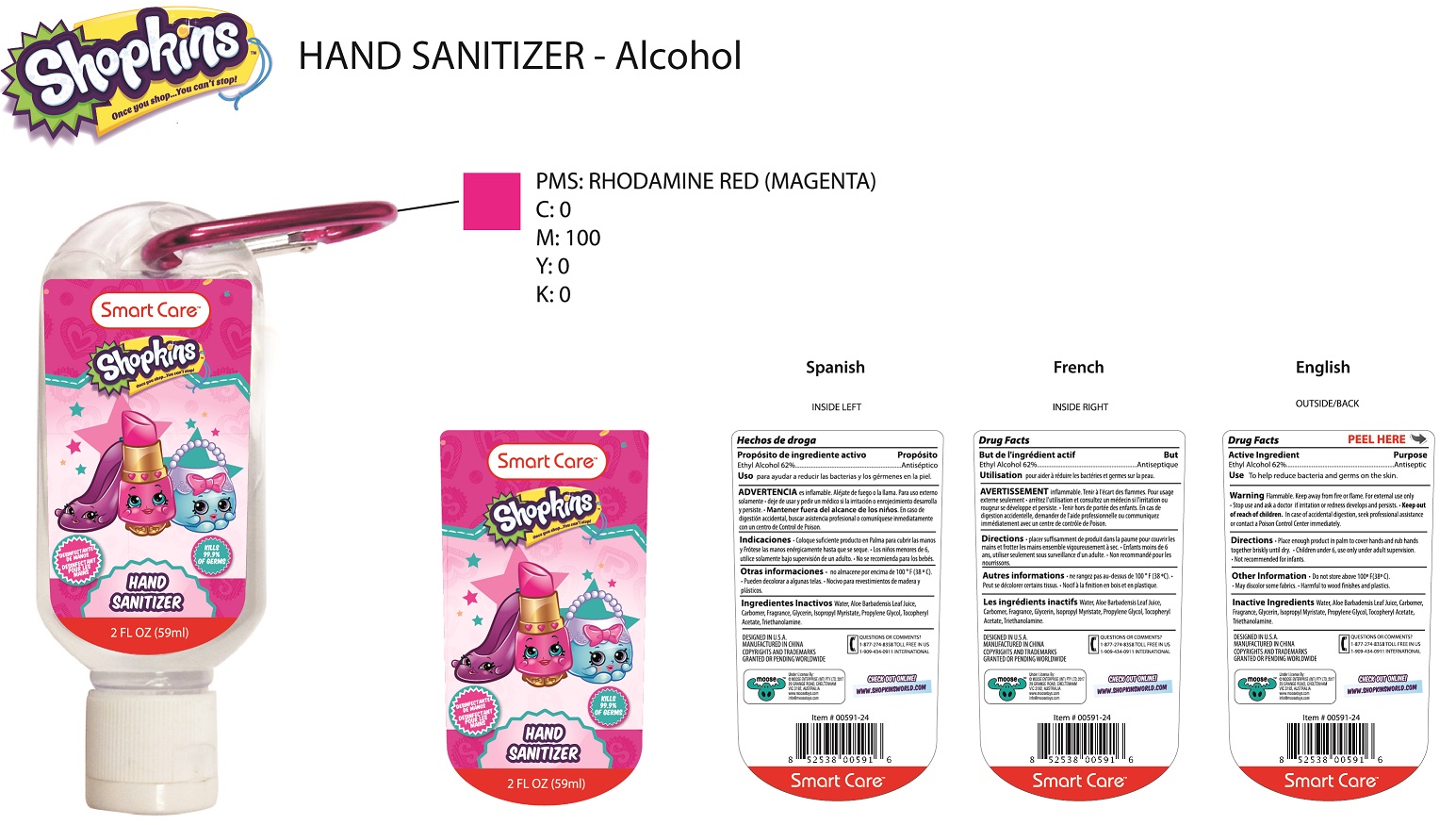 DRUG LABEL: SmartCare Shopkins
NDC: 50154-010 | Form: GEL
Manufacturer: Lantern Enterprises Ltd.
Category: otc | Type: HUMAN OTC DRUG LABEL
Date: 20171027

ACTIVE INGREDIENTS: ALCOHOL 62 mL/100 mL
INACTIVE INGREDIENTS: ALOE VERA LEAF; CARBOMER COPOLYMER TYPE A; GLYCERIN; ISOPROPYL MYRISTATE; PROPYLENE GLYCOL; .ALPHA.-TOCOPHEROL ACETATE; TROLAMINE; WATER

Active Ingredient

Ethyl Alcohol 62%

Purpose

Antiseptic

Keep out of reach of children. In case of accidental ingestion, seek professional assistance or contact a Poison Control Center right away.

Uses

To help reduce bacteria and germs on the skin.

Directions

- Place enough product in palm to cove rhands and rub hands briskly together until dry.
- Children under 6, use only under adult supervision.
- Not recommended for infants.

Warning

Flammable. Keep away from fire or flame. For external use only.

Stop use and ask a doctor if irritation or redness develops and persists.

Inactive ingredients

aloe barbadensis gel, carbomer, fragrance, glycerin, isopropyl myristate, propylene glycol, tocopheryl acetate, triethanolamine, water